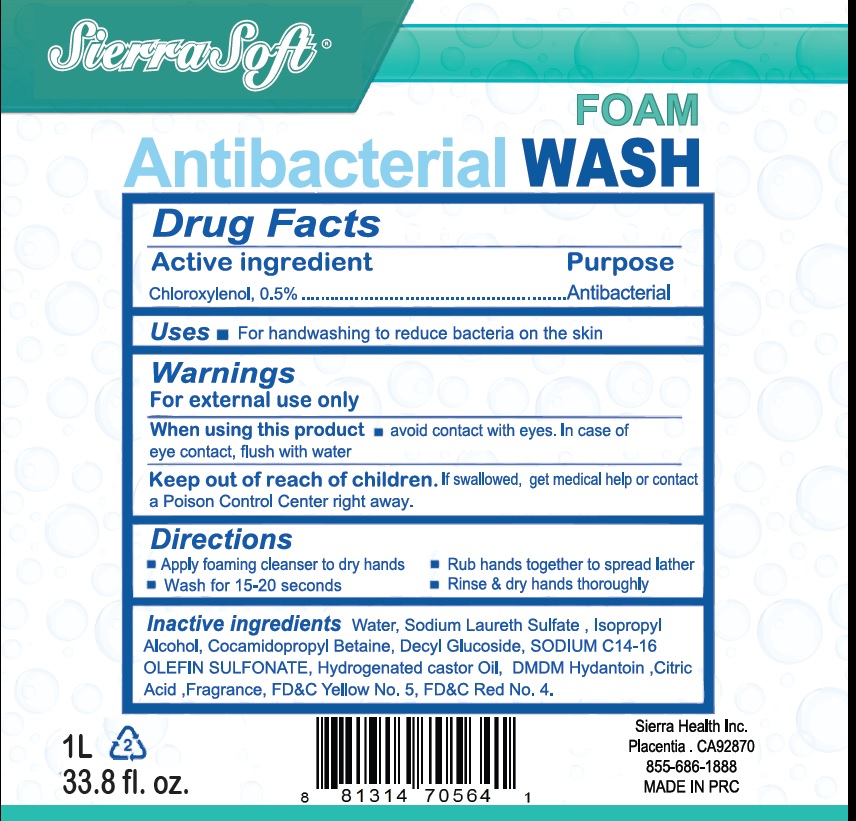 DRUG LABEL: Sierra Soft Antibacterial Wash
NDC: 70415-001 | Form: LIQUID
Manufacturer: CWGC LA Inc.
Category: otc | Type: HUMAN OTC DRUG LABEL
Date: 20250421

ACTIVE INGREDIENTS: CHLOROXYLENOL 5 g/1 L
INACTIVE INGREDIENTS: WATER; SODIUM LAURETH SULFATE; ISOPROPYL ALCOHOL; COCAMIDOPROPYL BETAINE; DECYL GLUCOSIDE; SODIUM C14-16 OLEFIN SULFONATE; HYDROGENATED CASTOR OIL; DMDM HYDANTOIN; CITRIC ACID MONOHYDRATE; FD&C YELLOW NO. 5; FD&C RED NO. 4

CWGC (as PLD) - Sierra Soft Antibacterial Wash Foam (70415-001)

Active ingredient

Chloroxylenol, 0.5%

Purpose

Antibacterial

Uses

For handwashing to reduce bacteria on the skin

Warnings

- For external use only

When using this product

- avoid contact with eyes. In case of eye contact, flush with water

Keep out of reach of children.

If swallowed, get medical help or contact a Poison Control Center right away.

Directions

- Apply foaming cleanser to dry hands
- Rub hands together to spread lather
- Wash for 15-20 seconds
- Rinse & dry hands thoroughly

Inactive ingredients

Water, Sodium Laureth Sulfate, Isopropyl Alcohol, Cocamidopropyl Betaine, Decyl Glucoside, SODIUM C14-16 OLEFIN SULFONATE, Hydrogenated castor Oil, DMDM Hydantoin, Citric Acid, Fragrance, FD&C Yellow No. 5, FD&C Red No. 4.